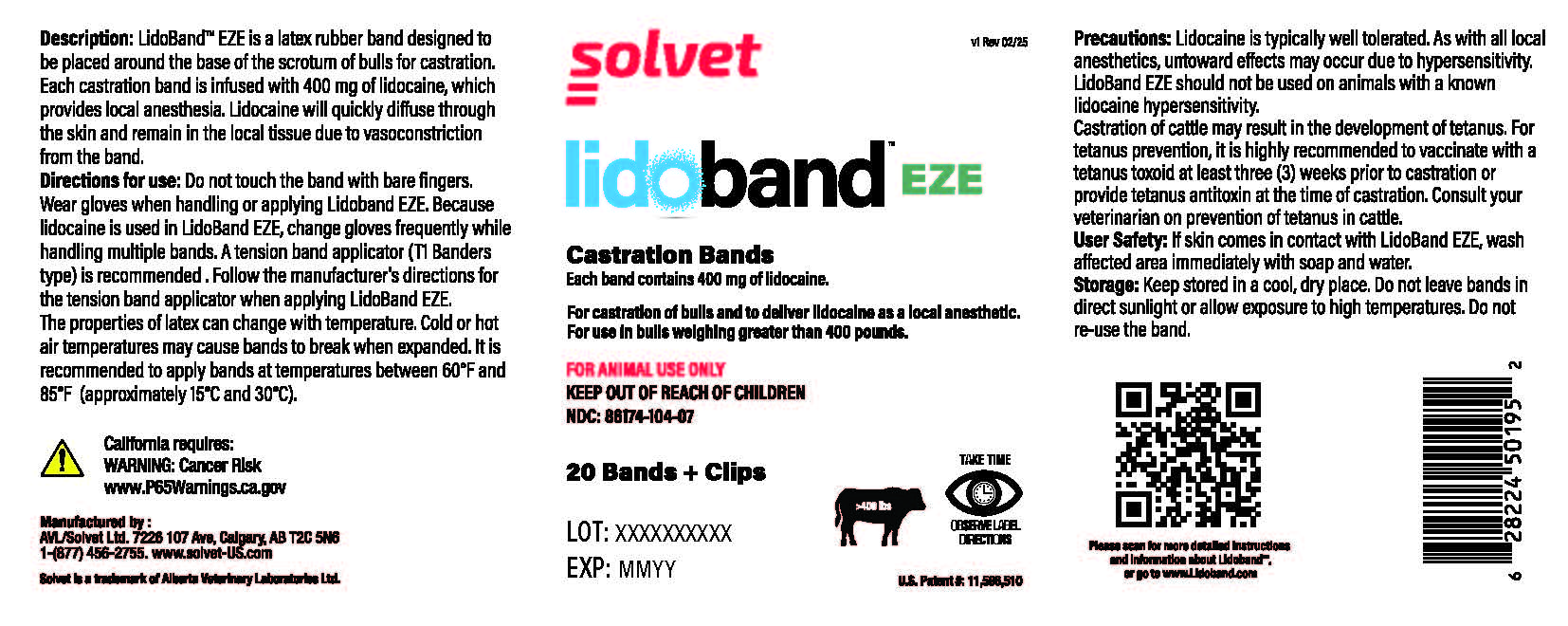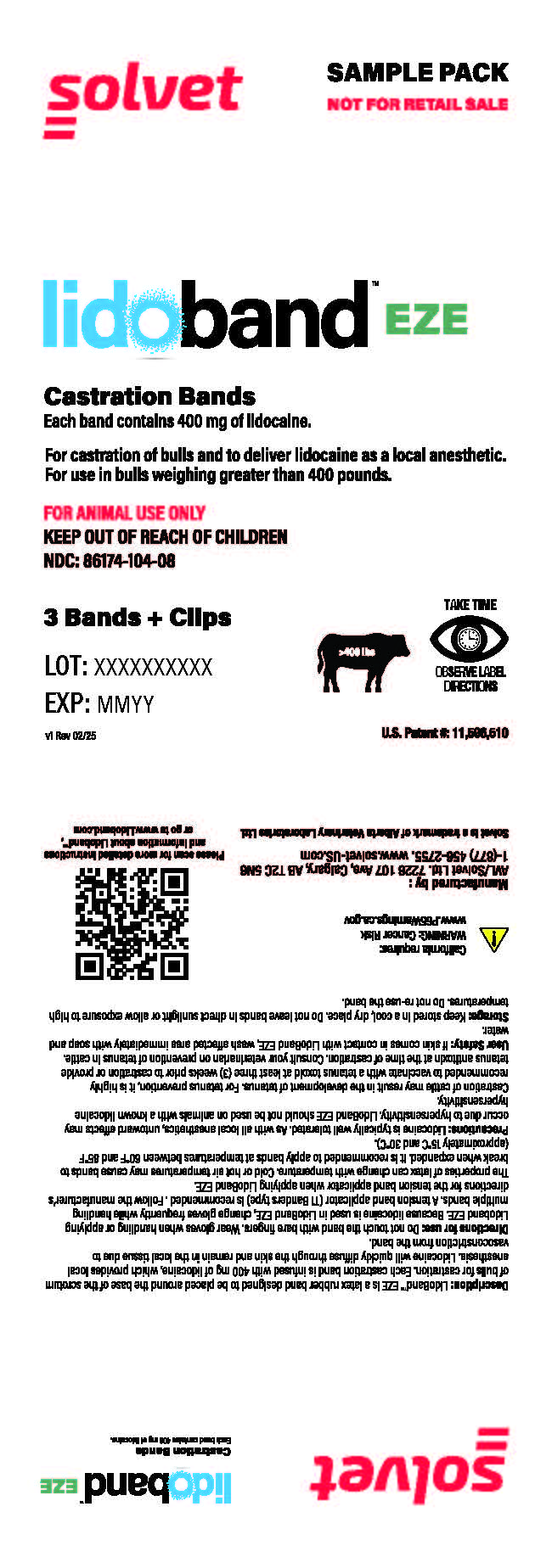 DRUG LABEL: LidoBand EZE
NDC: 86174-104 | Form: RING
Manufacturer: Alberta Veterinary Laboratories Ltd
Category: animal | Type: OTC ANIMAL DRUG LABEL
Date: 20251216

ACTIVE INGREDIENTS: LIDOCAINE 400 mg/1 1
INACTIVE INGREDIENTS: ISOPROPYL MYRISTATE 60 mg/1 1

LidoBand EZE

Description:

LidoBand™ EZE is a latex rubber band designed to be placed around the base of the scrotum of bulls for castration. Each castration band is infused with 400 mg of lidocaine, which provides local anesthesia. Lidocaine will quickly diffuse through the skin and remain in the local tissue due to vasoconstriction from the band.

Directions for Use:

Do not touch the band with bare fingers. Wear gloves when handling or applying Lidoband EZE. Because lidocaine is used in LidoBand EZE, change gloves frequently while handling multiple bands. A tension band applicator (TI Banders type) is recommended. Follow the manufacturer's directions for the tension band applicator when applying LidoBand EZE. The properties of latex can change with temperature. Cold or hot air temperatures may cause bands to break when expanded. It is recommended to apply bands at temperatures between 60°F and 85°F (approximately 15°C and 30°C).

Precautions:

Lidocaine is typically well tolerated. As with all local anesthetics, untoward effects may occur due to hypersensitivity. LidoBand EZE should not be used on animals with a known lidocaine hypersensitivity. Castration of cattle may result in the development of tetanus. For tetanus prevention, it is highly recommended to vaccinate with a tetanus toxoid at least three (3) weeks prior to castration or provide tetanus antitoxin at the time of castration. Consult your veterinarian on prevention of tetanus in cattle.

User Safety:

If skin comes in contact with LidoBand EZE, wash affected area immediately with soap and water.

Storage:

Keep stored in a cool, dry place. Do not leave bands in direct sunlight or allow exposure to high temperatures. Do not re-use the band.

OTHER SAFETY INFORMATION

For castration of bulls and to deliver lidocaine as a local anesthetic.
For use in bulls weighing greater than 400 pounds.
FOR ANIMAL USE ONLY
KEEP OUT OF REACH OF CHILDREN

LidoBand EZE Labels:

LidoBand EZE Jar Label

LidoBand EZE Sample Pack label